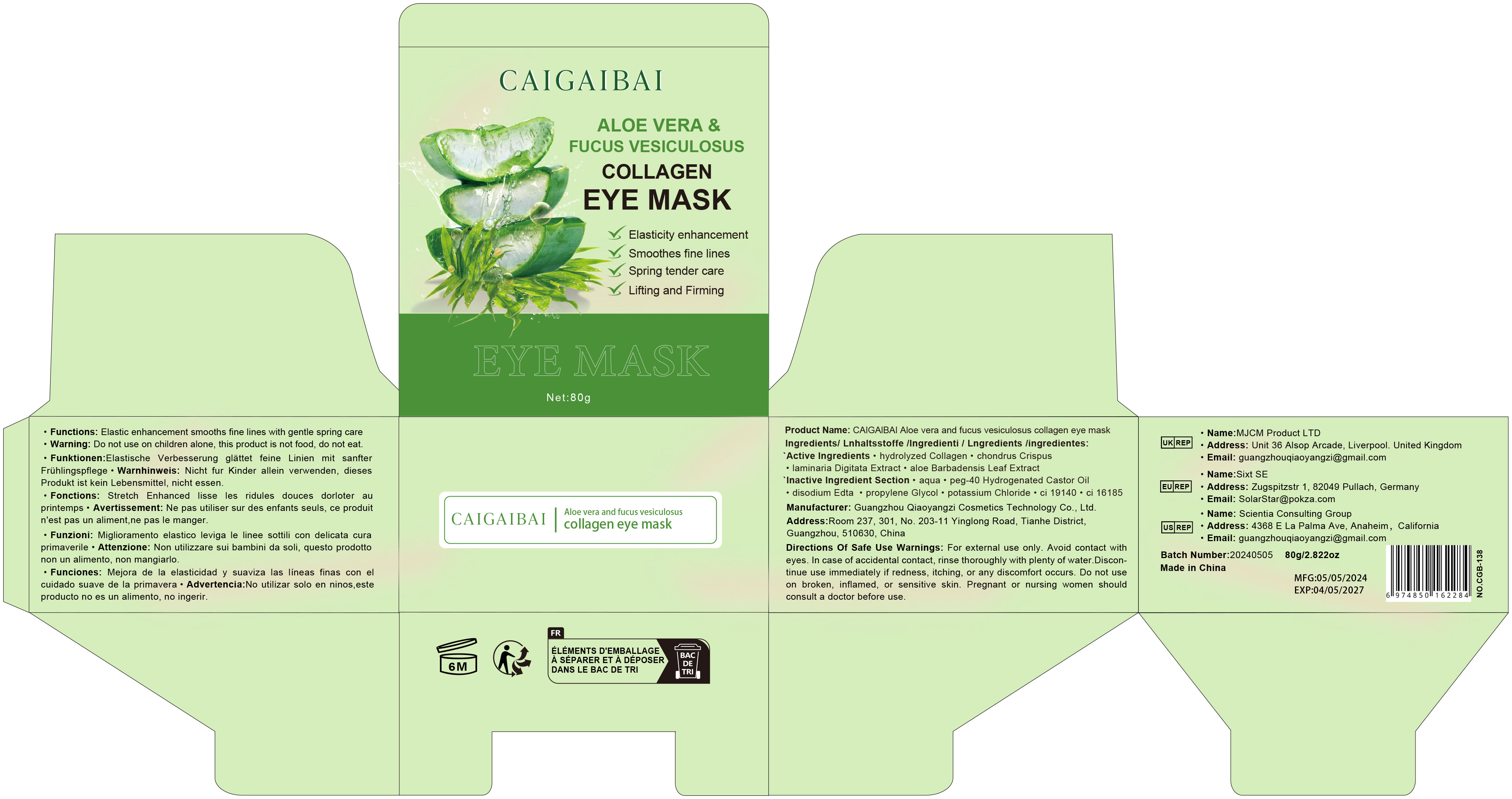 DRUG LABEL: Aloe vera and fucus vesiculosus collagen eye mask
NDC: 84751-138 | Form: EMULSION
Manufacturer: Guangzhou Qiaoyangzi Cosmetics Technology Co Ltd
Category: otc | Type: HUMAN OTC DRUG LABEL
Date: 20241020

ACTIVE INGREDIENTS: ALOE BARBADENSIS LEAF EXTRACT 0.85 g/100 g; HYDROLYZED SOY PROTEIN (ENZYMATIC; 2000 MW) 4 g/100 g; CHONDRUS CRISPUS 0.8 g/100 g; LAMINARIA DIGITATA EXTRACT 0.75 g/100 g
INACTIVE INGREDIENTS: EDETATE DISODIUM 0.3 g/100 g; CI 19140 0.05 g/100 g; POTASSIUM CHLORIDE 1.2 g/100 g; AQUA 79.85 g/100 g; PROPYLENE GLYCOL 2.15 g/100 g; PEG-40 HYDROGENATED CASTOR OIL 10 g/100 g; CI 16185 0.05 g/100 g

Active ingredients

Hydrolyzed Soy Protein 4.00%
Chondrus Crispus 0.80%
Laminaria Digitata Extract 0.75%
Aloe Barbadensis Leaf Extract 0.85%

INACTIVE INGREDIENT SECTION

Aqua 79.85%
PEG-40 Hydrogenated Castor Oil 10.00%
Disodium EDTA 0.30%
Propylene Glycol 2.15%
Potassium Chloride 1.20%
CI 19140 0.05%
CI 16185 0.05%

Purpose

Purpose: Used to firm and moisturize the skin around the eyes, reducing the appearance of fine lines and wrinkles, and improving skin elasticity and smoothness. Suitable for users looking to enhance the condition of their eye area.

Uses

Indications: Used to improve the firmness and smoothness of the eyelid area, reducing the appearance of fine lines and wrinkles; suitable for users looking to enhance the appearance of their eye area.
Usage: After cleansing the eyelid area, take one sheet of the eye mask and apply it directly to the eyelid, ensuring it adheres well. Use 1-2 times daily, once in the morning and once in the evening, for 15-20 minutes each time.

Warnings

For external use only. Avoid contact with eyes. In case of accidental contact, rinse thoroughly with plenty of water.
Discontinue use immediately if redness, itching, or any discomfort occurs.
Do not use on broken, inflamed, or sensitive skin.
Pregnant or nursing women should consult a doctor before use.

Stop use

Discontinue use immediately if the following occurs:
Skin redness, itching, or irritation worsens.
Experience any unusual discomfort after use.
Any adverse reaction or allergic symptoms appear on the skin.

Do not use

Do not use this product if:
You are allergic to any ingredient in this product.
There are open wounds, inflammation, or infection on the skin.
On sensitive, broken, or irritated skin.
You have skin conditions (such as eczema, psoriasis, etc.).

Keep out of reach of children!

This product should be kept out of the reach of children.
In case of accidental ingestion, seek medical help or contact a poison control center immediately.

Precautions for Use

For external use only; do not apply this product to the skin around the eyes.
Ensure hands are clean while applying to avoid contamination.
If using other eye products, consult a doctor or dermatologist before using this product.
Use as directed; do not overapply.

Instructions for Use

Clean the eyelid area, ensuring there is no residue from makeup or dirt.
Remove one sheet of the eye mask from the box.
Gently apply the eye mask to the eyelid, ensuring full adherence.
Recommended use for 15-20 minutes, then remove the eye mask.
After use, gently pat any remaining essence into the skin for better absorption.

DOSAGE & ADMINISTRATION SECTION

Dosage & Administration:

Use one sheet of the eye mask per application.
Use 1-2 times daily, once in the morning and once in the evening.
Recommended application time is 15-20 minutes.
Adjust usage frequency as needed to achieve optimal results.